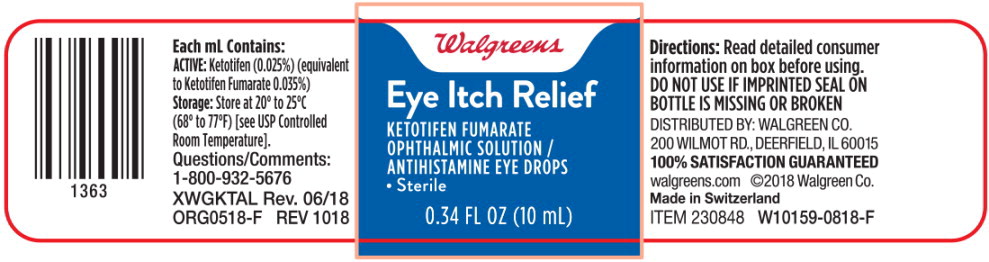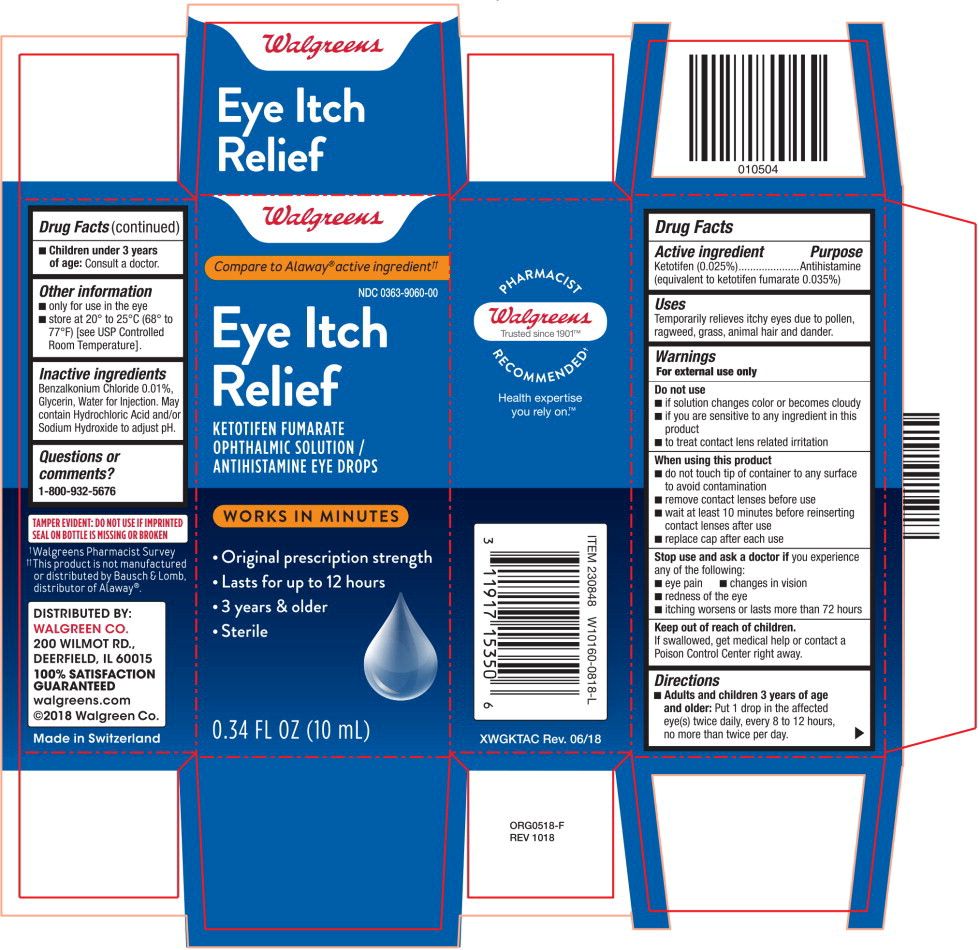 DRUG LABEL: Ketotifen Fumarate
NDC: 0363-9060 | Form: SOLUTION/ DROPS
Manufacturer: Walgreens
Category: otc | Type: HUMAN OTC DRUG LABEL
Date: 20220211

ACTIVE INGREDIENTS: ketotifen fumarate 0.25 mg/1 mL
INACTIVE INGREDIENTS: benzalkonium chloride; glycerin; water; hydrochloric acid; sodium hydroxide

Drug Facts

Active ingredient

Ketotifen (0.025%)

(equivalent to ketotifen fumarate 0.035%)

Purpose

Antihistamine

Use

Temporarily relieves itchy eyes due to pollen, ragweed, grass, animal hair and dander.

Warnings

For external use only

Do not use

- if solution changes color or becomes cloudy
- if you are sensitive to any ingredient in this product
- to treat contact lens related irritation

When using this product

- do not touch tip of container to any surface to avoid contamination
- remove contact lenses before use
- wait at least 10 minutes before reinserting contact lenses after use
- replace cap after each use

Stop use and ask a doctor if you experience any of the following:

- eye pain
- changes in vision
- redness of the eye
- itching worsens or lasts for more than 72 hours

Keep out of reach of children.

If swallowed, get medical help or contact a Poison Control Center right away.

Directions

- Adults and children 3 years of age and older:
  Put 1 drop in the affected eye(s) twice daily, every 8 to 12 hours, no more than twice per day.
- Children under 3 years of age:
  Consult a doctor.

Other information

- only for use in the eye
- store at 20° to 25°C (68° to 77°F) [see USP Controlled Room Temperature].

Inactive ingredients

Benzalkonium Chloride 0.01%, Glycerin, Water for Injection. May contain Hydrochloric Acid and/or Sodium Hydroxide to adjust pH.

Questions or Comments?

1-800-932-5676

Principal Display Panel Text for Container Label:

Walgreens Logo

Eye Itch Relief

KETOTIFEN FUMARATE
OPHTHALMIC SOLUTION /
ANTIHISTAMINE EYE DROPS

● Sterile

0.34 FL OZ (10 mL)

Principal Display Panel Text for Carton Label:

Walgreens Logo

Compare to Alaway® active ingredient††

Eye Itch

Relief

KETOTIFEN FUMARATE
OPHTHALMIC SOLUTION /
ANTIHISTAMINE EYE DROPS

WORKS IN MINUTES

- Original prescription strength
- Lasts for up to 12 hours
- 3 years & older
- Sterile

0.34 FL OZ (10 mL)